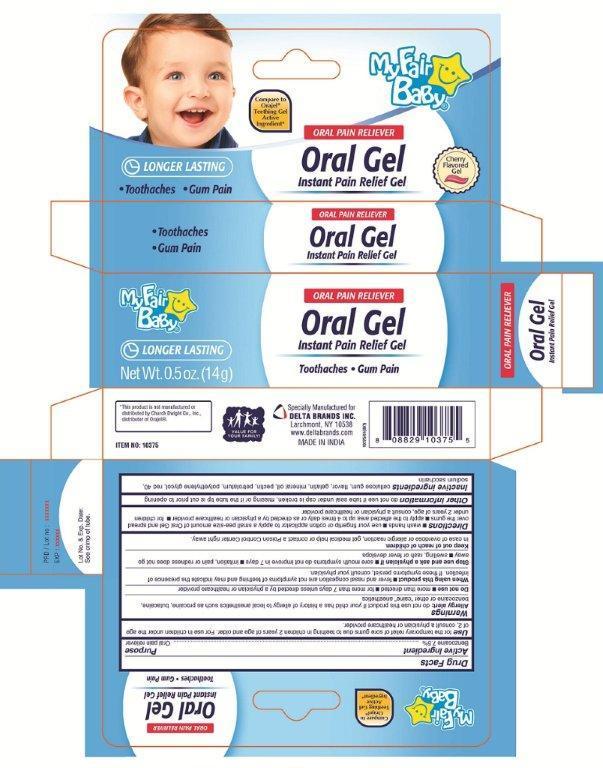 DRUG LABEL: My Fair Baby oral gel
NDC: 47046-180 | Form: GEL
Manufacturer: Anicare Pharmaceuticals Pvt. Ltd.
Category: otc | Type: HUMAN OTC DRUG LABEL
Date: 20201220

ACTIVE INGREDIENTS: BENZOCAINE 7.5 g/100 g
INACTIVE INGREDIENTS: CARBOXYMETHYLCELLULOSE SODIUM; GELATIN; MINERAL OIL; PECTIN; PETROLATUM; POLYETHYLENE GLYCOL 1000; POLYETHYLENE GLYCOL, UNSPECIFIED; FD&C RED NO. 40; SACCHARIN SODIUM

oral gel

Active Ingredient

Benzocaine 7.5%

Purpose

Oral Pain Reliever

Uses

for the temporary relief of sore gums due to teething in children 2 years of age and older. For use in children under the age of 2, consult a physician or healthcare provider.

Warnings

Allergy alert: do not use this product if your baby has a history of allergy to local anesthetics such as procaine, butacaine or other "caine" anesthetics

Do not use

■ more than directed ■ for more than 7 days unless directed by a physician or healthcare provider

When using this product

■ fever and nasal congestion are not symptoms of teething and may indicate the presence of infection. If these symptoms persist, consult your physician

Stop use and ask a physician if

sore mouth symptoms do not get better in 7 days ■ irritation, pain or redness does not go away ■ swelling, rash or fever develops

Keep out of reach of children

In case of overdose or allergic reaction get medical help or contact a Poison Control Center right away

Directions

■ wash your hands ■ use your fingertip or cotton applicator to apply a small pea-size amount of Oral Gel and spread over gums ■ apply to affected area up to 4 times daily or as directed by a physician or healthcare provider ■ for children under 2 years of age, consult a physician or health care provider

Other information

do not use if tube seal under cap is broken, missing or if the tube tip is cut prior to opening

Inactive ingredients

cellulose gum, flavor, gelatin, mineral oil, pectin, petrolatum, polyethylene glycol, red 40, sodium saccharin